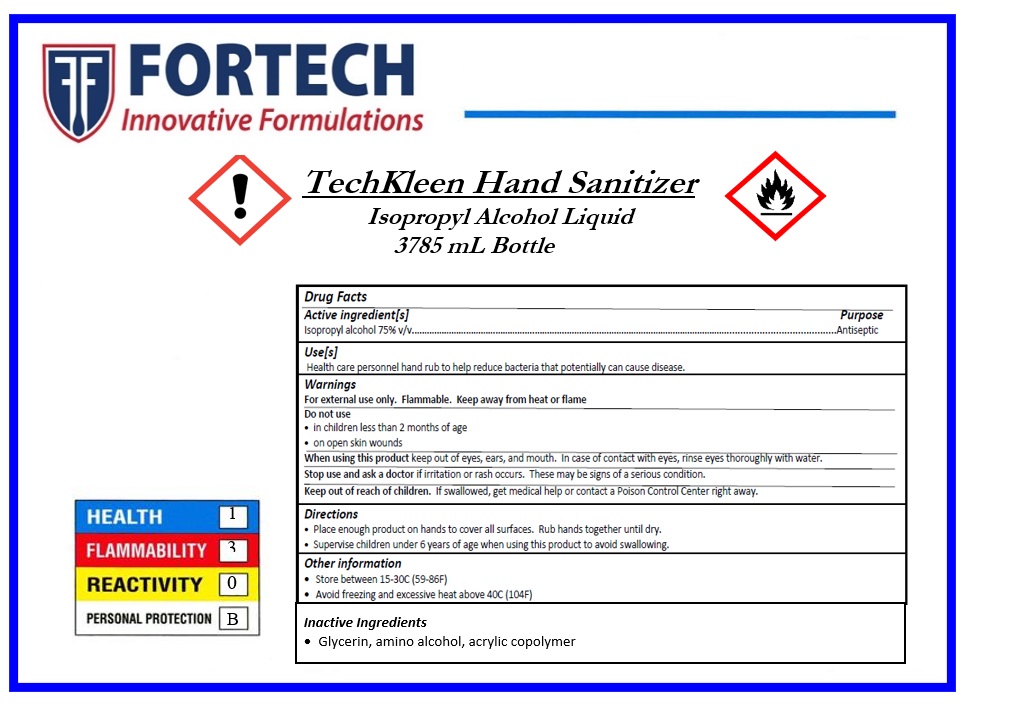 DRUG LABEL: TechKleen Hand Sanitizer
NDC: 78685-001 | Form: LIQUID
Manufacturer: Fortech Products, Inc.
Category: otc | Type: HUMAN OTC DRUG LABEL
Date: 20200615

ACTIVE INGREDIENTS: ISOPROPYL ALCOHOL 75 mL/100 mL
INACTIVE INGREDIENTS: GLYCERIN; AMINOMETHYLPROPANOL; POLYACRYLIC ACID (8000 MW)

TechKleen Hand Sanitizer

Active ingredient[s]

Isopropyl alcohol 75% v/v

Purpose

Antiseptic

Use[s]

Health care personnel hand rub to help reduce bacteria that potentially can cause disease.

Warnings

For external use only. Flammable. Keep away from heat or flame

Do not use

- in children less than 2 months of age
- on open skin wounds

When using this product keep out of eyes, ears, and mouth. In case of contact with eyes, rinse eyes thoroughly with water.

Stop use and ask a doctor if irritation or rash occurs. These may be signs of a serious condition.

Keep out of reach of children. If swallowed, get medical help or contact a Poison Control Center right away.

Directions

- Place enough product on hands to cover all surfaces. Rub hands together until dry.
- Supervise children under 6 years of age when using this product to avoid swallowing.

Other information

- Store between 15-30°C (59-86°F)
- Avoid freezing and excessive heat above 40°C (104°F)

Inactive ingredients

glycerin, amino alcohol, acrylic copolymer

FORTECH

Innovative Formulations

7600 Kensington Ct. Brighton, MI 48116

Phone: (248) 446-9500 Fax: 248-446-9500

For chemical emergency or questions,call

800-252-6516